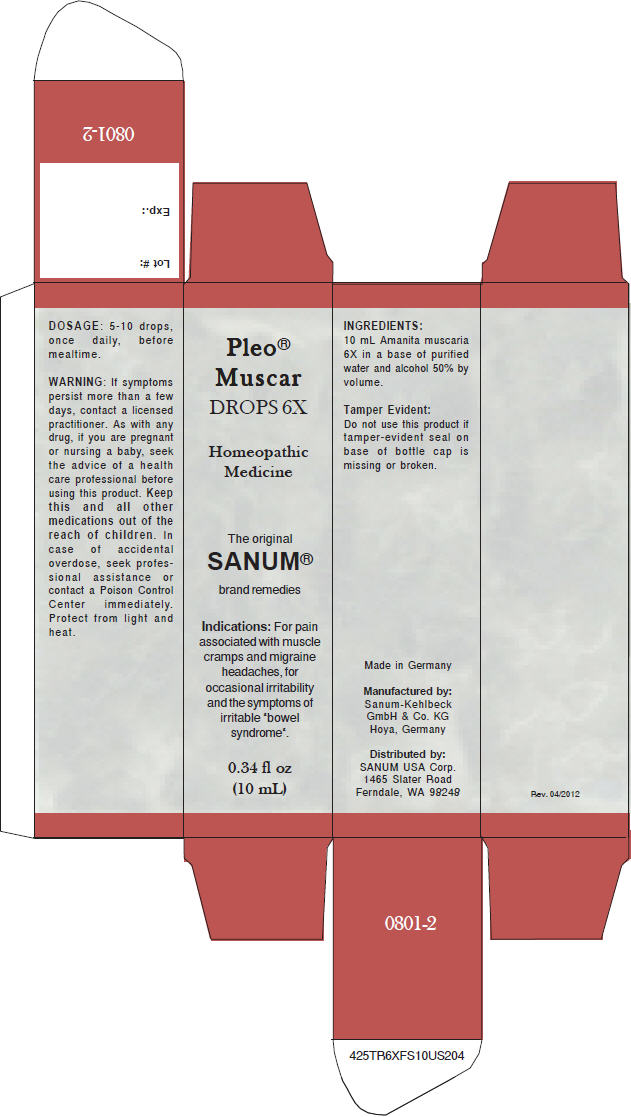 DRUG LABEL: Pleo Muscar
NDC: 60681-0801 | Form: LIQUID
Manufacturer: Sanum-Kehlbeck GmbH & Co. KG
Category: homeopathic | Type: HUMAN OTC DRUG LABEL
Date: 20120626

ACTIVE INGREDIENTS: AMANITA MUSCARIA WHOLE 6 [hp_X]/10 mL
INACTIVE INGREDIENTS: WATER; ALCOHOL

Pleo® Muscar DROPS 6X

PURPOSE

Homeopathic Medicine

Indications

For pain associated with muscle cramps and migraine headaches, for occasional irritability and the symptoms of irritable "bowel syndrome".

ACTIVE INGREDIENT

INGREDIENTS

10 mL Amanita muscaria 6X in a base of purified water and alcohol 50% by volume.

Tamper Evident

Do not use this product if tamper-evident seal on base of bottle cap is missing or broken.

DOSAGE

5-10 drops, once daily, before mealtime.

WARNING

ASK DOCTOR

If symptoms persist more than a few days, contact a licensed practitioner.

PREGNANCY OR BREAST FEEDING

As with any drug, if you are pregnant or nursing a baby, seek the advice of a health care professional before using this product.

KEEP OUT OF REACH OF CHILDREN

Keep this and all other medications out of the reach of children. In case of accidental overdose, seek professional assistance or contact a Poison Control Center immediately.

STORAGE AND HANDLING

Protect from light and heat.

Manufactured by: Sanum-Kehlbeck GmbH & Co. KG Hoya, Germany

Distributed by: SANUM USA Corp. 1465 Slater Road Ferndale, WA 98248

PRINCIPAL DISPLAY PANEL - 10 mL Bottle Carton

Pleo®
Muscar
DROPS 6X

Homeopathic
Medicine

The original
SANUM®

brand remedies

Indications: For pain
associated with muscle
cramps and migraine
headaches, for
occasional irritability
and the symptoms of
irritable "bowel
syndrome".

0.34 fl oz
(10 mL)